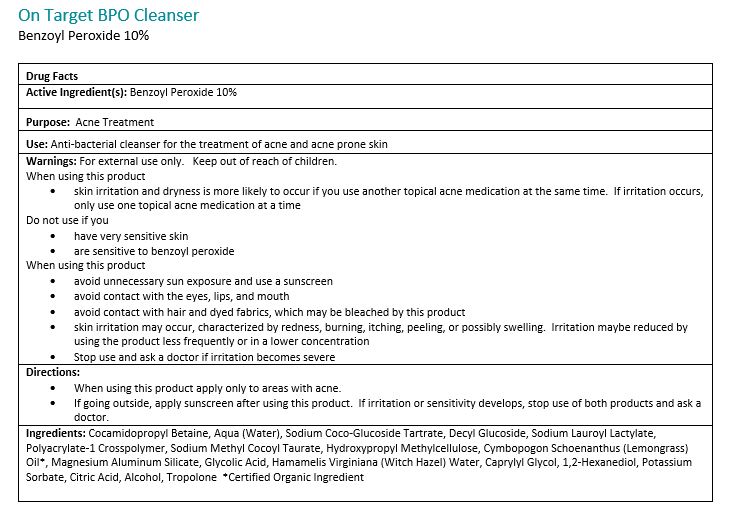 DRUG LABEL: On Target
NDC: 66915-437 | Form: GEL
Manufacturer: CoValence, Inc.
Category: otc | Type: HUMAN OTC DRUG LABEL
Date: 20150420

ACTIVE INGREDIENTS: BENZOYL PEROXIDE 0.102 g/1 g
INACTIVE INGREDIENTS: DECYL GLUCOSIDE 1 g/1 g; Water 1 g/1 g; SODIUM LAUROYL LACTYLATE 1 g/1 g; SODIUM METHYL COCOYL TAURATE 1 g/1 g; WITCH HAZEL 1 g/1 g; 1,2-HEXANEDIOL 1 g/1 g; COCAMIDOPROPYL BETAINE 1 g/1 g; CYMBOPOGON SCHOENANTHUS LEAF 1 g/1 g; MAGNESIUM ALUMINUM SILICATE 1 g/1 g; GLYCOLIC ACID 1 g/1 g; CAPRYLYL GLYCOL 1 g/1 g; POTASSIUM SORBATE 1 g/1 g; CITRIC ACID MONOHYDRATE 1 g/1 g; ALCOHOL 1 g/1 g; TROPOLONE 1 g/1 g

OTC Drug Facts On Target BPO Cleanser

Principal Display Panel

Active Ingredients:

Benzoyl Peroxide 10%

Purpose:

Acne Treatment

Warnings:

Children under 12 years of age: Do not use, consult a physician.

Warnings:

For external use only. Avoide contact with eyes, eyelids, lips and mucous membranes. If accidental contact occurs, rinse with water. Contact with any colored material (including hair and fabric) may result in blaching or discoloration. If exceessive irritation develops, disconintue use and consult your physician.

Directions:

Adults and children 12 years of age or older: Apply to the affected are no more than 3 to 4 times daily.

Ingredients:

Cocamidopropyl Betain, Aqua (Water), Sodium Coco-Glucoside Tartrate, Decyl Glucoside, Sodium Lauroyl Lactylate, Polyacrylate-1 Crosspolymer, Sodium Methyl Cocoyl Taurate, Hydroxypropyl Methylcellulose, Cymbopogon Schoenathus (Lemongrass) Oil*, Magnesium Aluminum Silicate, Glycolid Acid, Hamamelis Virginiana (Witch Hazel) Water, Caprylyl Glycol, 1,2-Hexanediol, Potassium Sorbate, Citric Acid, Alcohol, Tropolone
*Certified Organic

Uses:

Antibacterial cleanser for the treatment of acne and acne prone skin.